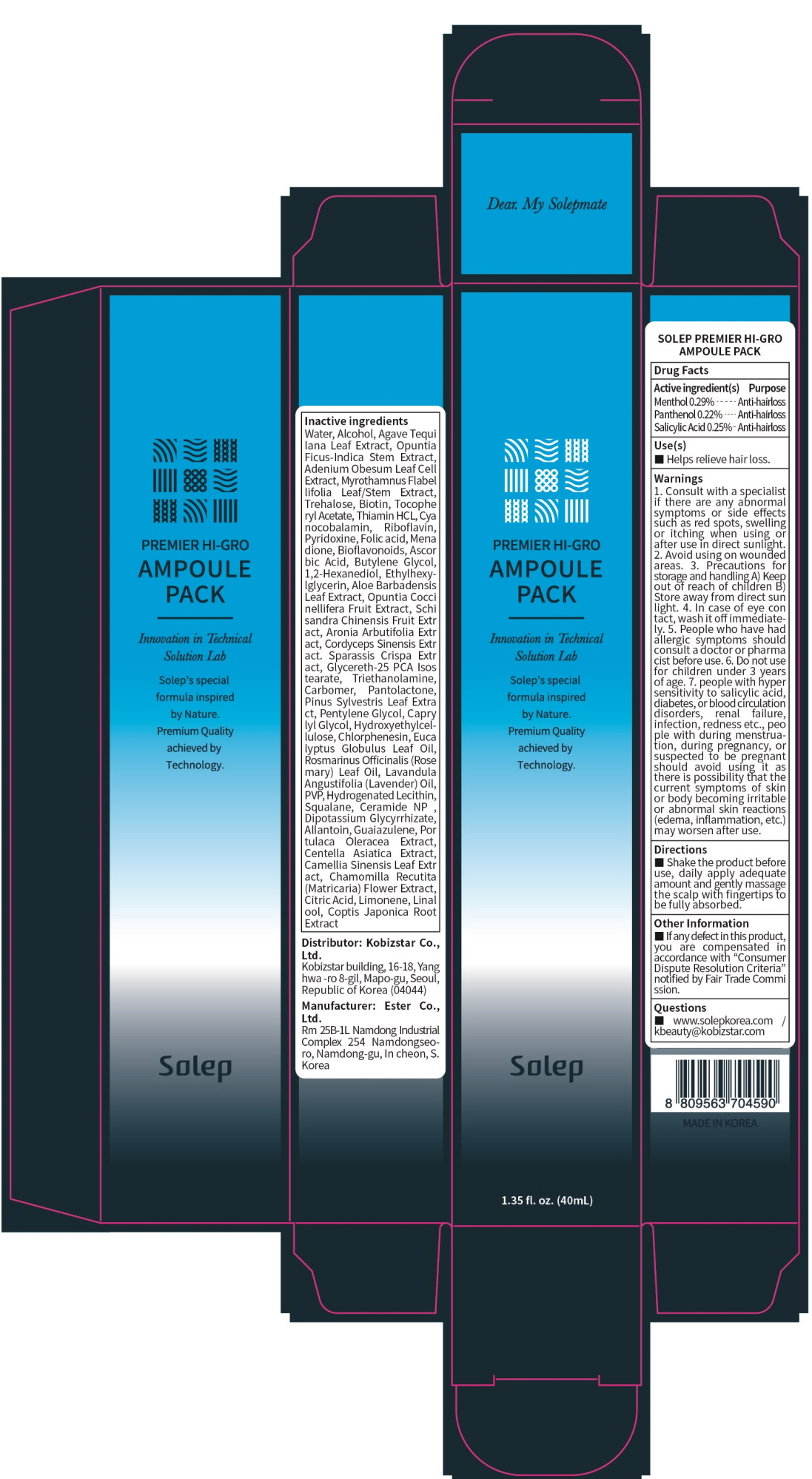 DRUG LABEL: SOLEP PREMIER HI GRO AMPOULE PACK
NDC: 81077-030 | Form: LIQUID
Manufacturer: Kobizstar Co., Ltd.
Category: otc | Type: HUMAN OTC DRUG LABEL
Date: 20201117

ACTIVE INGREDIENTS: Panthenol 0.20 g/40 mL; Menthol 0.11 g/40 mL; Salicylic Acid 0.10 g/40 mL
INACTIVE INGREDIENTS: Water; Alcohol

ACTIVE INGREDIENT(S)

Panthenol 0.50%
Menthol 0.29%
Salicylic Acid 0.25%

INACTIVE INGREDIENTS

Water, Alcohol, Agave Tequilana Leaf Extract, Opuntia Ficus-Indica Stem Extract, Adenium Obesum Leaf Cell Extract, Myrothamnus Flabellifolia Leaf/Stem Extract, Trehalose, Biotin, Tocopheryl Acetate, Thiamin HCL, Cyanocobalamin, Riboflavin, Pyridoxine, Folic acid, Menadione, Bioflavonoids, Ascorbic Acid, Butylene Glycol, 1,2-Hexanediol, Ethylhexylglycerin, Aloe Barbadensis Leaf Extract, Opuntia Coccinellifera Fruit Extract, Schisandra Chinensis Fruit Extract, Aronia Arbutifolia Extract, Cordyceps Sinensis Extract. Sparassis Crispa Extract, Glycereth-25 PCA Isostearate, Triethanolamine, Carbomer, Pantolactone, Pinus Sylvestris Leaf Extract, Pentylene Glycol, Caprylyl Glycol, Hydroxyethylcellulose, Chlorphenesin, Eucalyptus Globulus Leaf Oil, Rosmarinus Officinalis (Rosemary) Leaf Oil, Lavandula Angustifolia (Lavender) Oil, PVP, Hydrogenated Lecithin, Squalane, Ceramide NP , Dipotassium Glycyrrhizate, Allantoin, Guaiazulene, Portulaca Oleracea Extract, Centella Asiatica Extract, Camellia Sinensis Leaf Extract, Chamomilla Recutita (Matricaria) Flower Extract, Citric Acid, Limonene, Linalool, Coptis Japonica Root Extract

PURPOSE

Anti-hairloss

WARNINGS

1. Consult with a specialist if there are any abnormal symptoms or side effects such as red spots, swelling or itching when using or after use in direct sunlight. 2. Avoid using on wounded areas. 3. Precautions for storage and handling A) Keep out of reach of children B) Store away from direct sunlight. 4. In case of eye contact, wash it off immediately. 5. People who have had allergic symptoms should consult a doctor or pharmacist before use. 6. Do not use for children under 3 years of age. 7. people with hypersensitivity to salicylic acid, diabetes, or blood circulation disorders, renal failure, infection, redness etc., people with during menstruation, during pregnancy, or suspected to be pregnant should avoid using it as there is possibility that the current symptoms of skin or body becoming irritable or abnormal skin reactions(edema, inflammation, etc.) may worsen after use.

KEEP OUT OF REACH OF CHILDREN

Use(s)

■ Helps relieve hair loss.

Directions

■ Shake the product before use, daily apply adequate amount and gently massage the scalp with fingertips to be fully absorbed.

Other Information

■ If any defect in this product, you are compensated in accordance with “Consumer Dispute Resolution Criteria” notified by Fair Trade Commission.

Questions

■ www.solepkorea.com / kbeauty@kobizstar.com